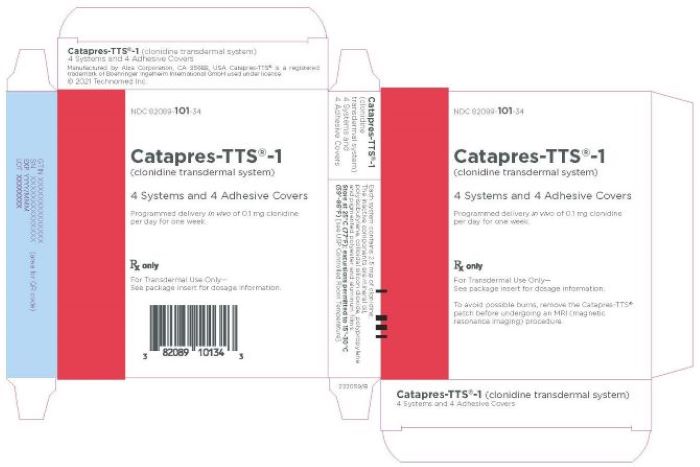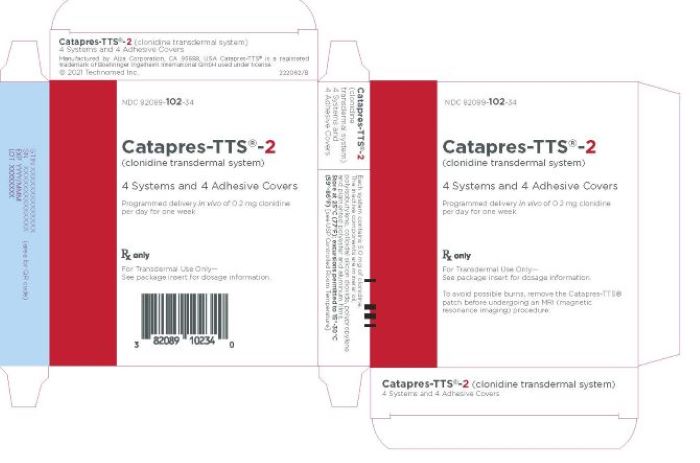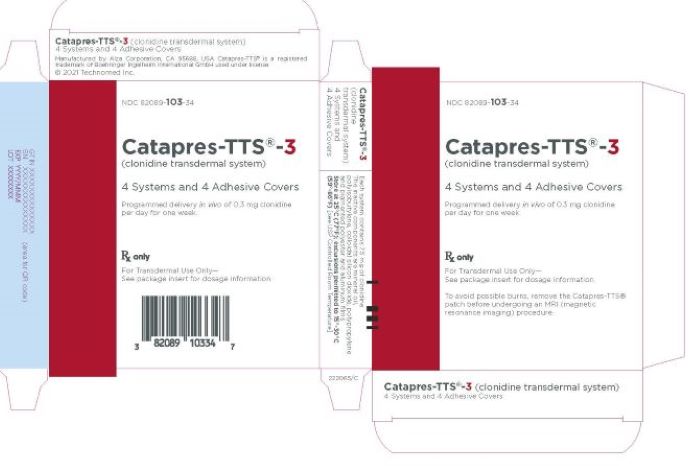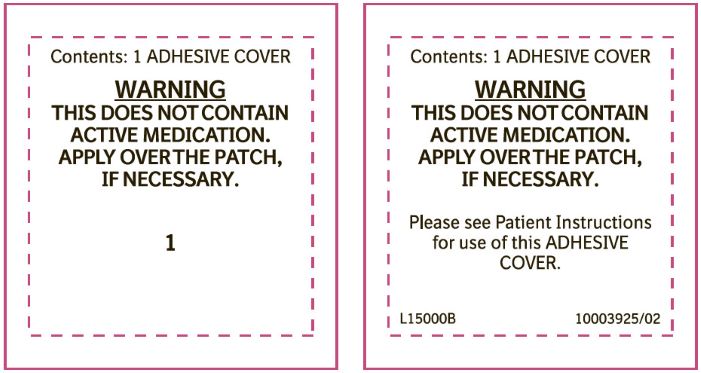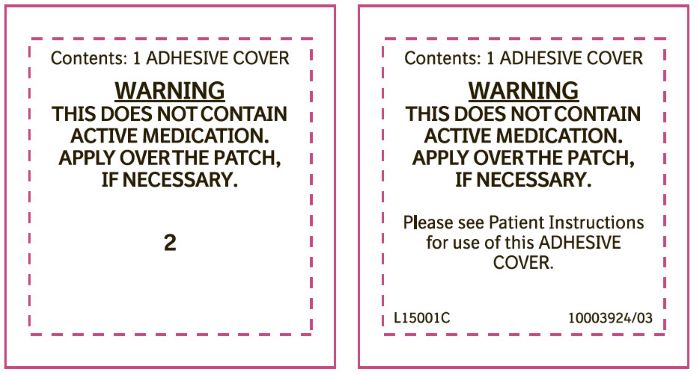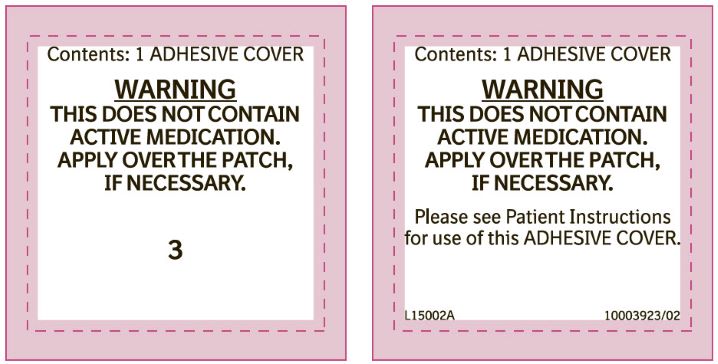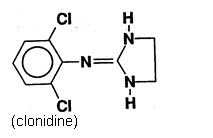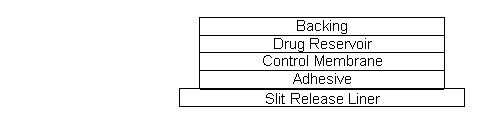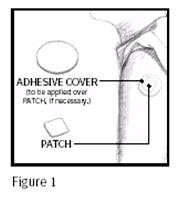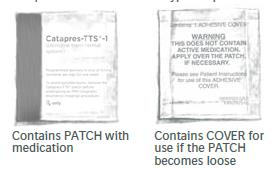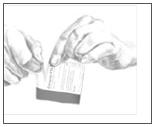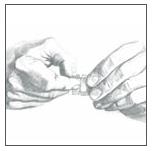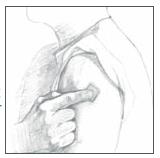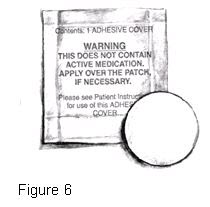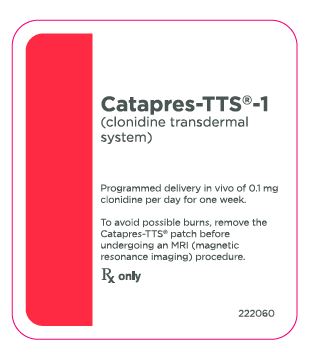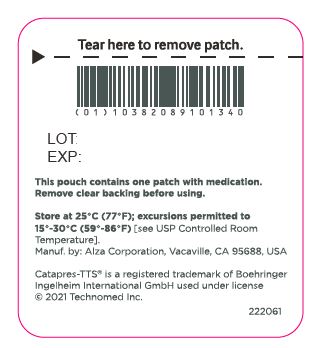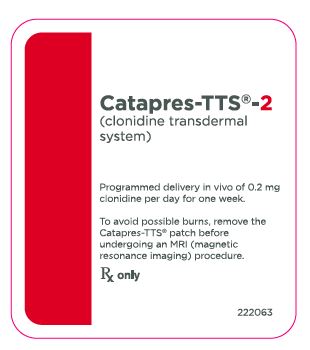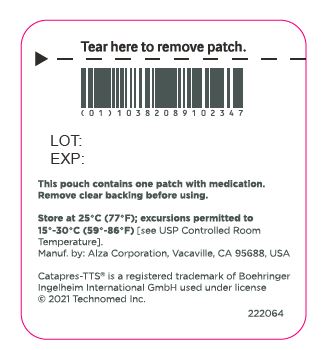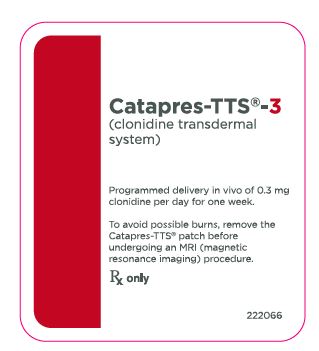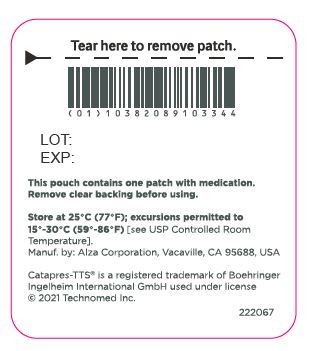 DRUG LABEL: Catapres-TTS-1
NDC: 82089-101 | Form: PATCH
Manufacturer: Technomed Inc.
Category: prescription | Type: HUMAN PRESCRIPTION DRUG LABEL
Date: 20241011

ACTIVE INGREDIENTS: CLONIDINE 0.1 mg/1 d
INACTIVE INGREDIENTS: MINERAL OIL; POLYISOBUTYLENE (1100000 MW); POLYISOBUTYLENE (35000 MW); SILICON DIOXIDE

Catapres-TTS®
(clonidine transdermal system)
Catapres-TTS® -1
Catapres-TTS® -2
Catapres-TTS® -3

Programmed delivery in vivo of 0.1, 0.2, or 0.3 mg clonidine per day, for one week.

Rx only

Prescribing Information

DESCRIPTION

Catapres‑TTS® (clonidine transdermal system) is a transdermal system providing continuous systemic delivery of clonidine for 7 days at an approximately constant rate. Clonidine is a centrally acting alpha‑agonist hypotensive agent. It is an imidazoline derivative with the chemical name 2, 6‑dichloro‑N‑2‑imidazolidinylidenebenzenamine and has the following chemical structure:

System Structure and Components

Catapres‑TTS® is a multi-layered film, 0.2 mm thick, containing clonidine as the active agent. The system areas are 3.5 cm^2 (Catapres‑TTS®‑1), 7.0 cm^2 (Catapres‑TTS®‑2) and 10.5 cm^2 (Catapres‑TTS®‑3) and the amount of drug released is directly proportional to the area (see Release Rate Concept). The composition per unit area is the same for all three doses.

Proceeding from the visible surface towards the surface attached to the skin, there are four consecutive layers: 1) a backing layer of pigmented polyester and aluminum film; 2) a drug reservoir of clonidine, mineral oil, polyisobutylene, and colloidal silicon dioxide; 3) a microporous polypropylene membrane that controls the rate of delivery of clonidine from the system to the skin surface; 4) an adhesive formulation of clonidine, mineral oil, polyisobutylene, and colloidal silicon dioxide. Prior to use, a protective slit release liner of polyester that covers the adhesive layer is removed.

Cross Section of the System:

Release Rate Concept

Catapres‑TTS® (clonidine transdermal system) is programmed to release clonidine at an approximately constant rate for 7 days. The energy for drug release is derived from the concentration gradient existing between a saturated solution of drug in the system and the much lower concentration prevailing in the skin. Clonidine flows in the direction of the lower concentration at a constant rate, limited by the rate‑controlling membrane, so long as a saturated solution is maintained in the drug reservoir.

Following system application to intact skin, clonidine in the adhesive layer saturates the skin site below the system. Clonidine from the drug reservoir then begins to flow through the rate‑controlling membrane and the adhesive layer of the system into the systemic circulation via the capillaries beneath the skin. Therapeutic plasma clonidine levels are achieved 2 to 3 days after initial application of Catapres‑TTS®.

The 3.5, 7.0, and 10.5 cm^2 systems deliver 0.1, 0.2, and 0.3 mg of clonidine per day, respectively. To ensure constant release of drug for 7 days, the total drug content of the system is higher than the total amount of drug delivered. Application of a new system to a fresh skin site at weekly intervals continuously maintains therapeutic plasma concentrations of clonidine. If the Catapres‑TTS® is removed and not replaced with a new system, therapeutic plasma clonidine levels will persist for about 8 hours and then decline slowly over several days. Over this time period, blood pressure returns gradually to pretreatment levels.

CLINICAL PHARMACOLOGY

Clonidine stimulates alpha‑adrenoreceptors in the brain stem. This action results in reduced sympathetic outflow from the central nervous system and in decreases in peripheral resistance, renal vascular resistance, heart rate, and blood pressure. Renal blood flow and glomerular filtration rate remain essentially unchanged. Normal postural reflexes are intact; therefore, orthostatic symptoms are mild and infrequent.

Acute studies with clonidine hydrochloride in humans have demonstrated a moderate reduction (15% to 20%) of cardiac output in the supine position with no change in the peripheral resistance; at a 45° tilt there is a smaller reduction in cardiac output and a decrease of peripheral resistance.

During long‑term therapy, cardiac output tends to return to control values, while peripheral resistance remains decreased. Slowing of the pulse rate has been observed in most patients given clonidine, but the drug does not alter normal hemodynamic responses to exercise.

Tolerance to the antihypertensive effect may develop in some patients, necessitating a reevaluation of therapy.

Other studies in patients have provided evidence of a reduction in plasma renin activity and in the excretion of aldosterone and catecholamines. The exact relationship of these pharmacologic actions to the antihypertensive effect of clonidine has not been fully elucidated.

Clonidine acutely stimulates the release of growth hormone in children as well as adults but does not produce a chronic elevation of growth hormone with long‑term use.

Pharmacokinetics

Catapres‑TTS® delivers clonidine at an approximately constant rate for 7 days. The absolute bioavailability of clonidine from the Catapres‑TTS® dosage form is approximately 60%. Steady-state clonidine plasma levels are obtained within 3 days after transdermal application to the upper outer arm and increase linearly with increasing size of the transdermal patch. Mean steady-state plasma concentrations with the 3.5 cm^2, 7.0 cm^2 and 10.5 cm^2 systems are approximately 0.4 ng/mL, 0.8 ng/mL, and 1.1 ng/mL, respectively. Similar clonidine steady-state concentrations are reached after application to the chest. Steady-state clonidine plasma levels remain constant after removal of one system and application of a new system of the same size.

Following intravenous administration clonidine displays biphasic disposition with a distribution half-life of about 20 minutes and an elimination half-life ranging from 12 to 16 hours. The half-life increases up to 41 hours in patients with severe impairment of renal function. Clonidine has a total clearance of 177 mL/min and a renal clearance of 102 mL/min. The apparent volume of distribution (Vz) of clonidine is 197 L (2.9 L/kg). Clonidine crosses the placental barrier. It has been shown to cross the blood brain barrier in rats.

Following oral administration, about 40% to 60% of the absorbed dose is recovered in the urine as unchanged drug within 24 hours. About 50% of the absorbed dose is metabolized in the liver.

After removal of the Catapres‑TTS®, clonidine plasma concentrations decline slowly with a half-life of approximately 20 hours.

INDICATIONS AND USAGE

Catapres‑TTS® is indicated in the treatment of hypertension. It may be employed alone or concomitantly with other antihypertensive agents.

CONTRAINDICATIONS

Catapres‑TTS® should not be used in patients with known hypersensitivity to clonidine or to any other component of the transdermal system.

WARNINGS

Withdrawal

Patients should be instructed not to discontinue therapy without consulting their physician. Sudden cessation of clonidine treatment has, in some cases, resulted in symptoms such as nervousness, agitation, headache, tremor, and confusion accompanied or followed by a rapid rise in blood pressure and elevated catecholamine concentrations in the plasma. The likelihood of such reactions to discontinuation of clonidine therapy appears to be greater after administration of higher doses or continuation of concomitant beta‑blocker treatment and special caution is therefore advised in these situations. Rare instances of hypertensive encephalopathy, cerebrovascular accidents and death have been reported after clonidine withdrawal. When discontinuing therapy with Catapres, the physician should reduce the dose gradually over 2 to 4 days to avoid withdrawal symptomatology.

An excessive rise in blood pressure following discontinuation of Catapres‑TTS® therapy can be reversed by administration of oral clonidine hydrochloride or by intravenous phentolamine. If therapy is to be discontinued in patients receiving a beta‑blocker and clonidine concurrently, the beta‑blocker should be withdrawn several days before the gradual discontinuation of Catapres‑TTS®.

PRECAUTIONS

General

In patients who have developed localized contact sensitization to Catapres‑TTS®, continuation of Catapres‑TTS® or substitution of oral clonidine hydrochloride therapy may be associated with development of a generalized skin rash.

In patients who develop an allergic reaction to Catapres‑TTS®, substitution of oral clonidine hydrochloride may also elicit an allergic reaction (including generalized rash, urticaria, or angioedema).

The sympatholytic action of clonidine may worsen sinus node dysfunction and atrioventricular (AV) block, especially in patients taking other sympatholytic drugs. There are post-marketing reports of patients with conduction abnormalities and/or taking other sympatholytic drugs who developed severe bradycardia requiring IV atropine, IV isoproterenol and temporary cardiac pacing while taking clonidine.

In hypertension caused by pheochromocytoma, no therapeutic effect of Catapres‑TTS® can be expected.

In rare instances, loss of blood pressure control has been reported in patients using Catapres‑TTS® according to the instructions for use.

Perioperative Use

Catapres‑TTS® should not be interrupted during the surgical period. Blood pressure should be carefully monitored during surgery and additional measures to control blood pressure should be available if required. Physicians considering starting Catapres‑TTS® therapy during the perioperative period must be aware that therapeutic plasma clonidine levels are not achieved until 2 to 3 days after initial application of Catapres-TTS® (see DOSAGE AND ADMINISTRATION).

Defibrillation or Cardioversion

The clonidine transdermal systems should be removed before attempting defibrillation or cardioversion because of the potential for altered electrical conductivity which may increase the risk of arcing, a phenomenon associated with the use of defibrillators.

MRI

Skin burns have been reported at the patch site in several patients wearing an aluminized transdermal system during a magnetic resonance imaging scan (MRI). Because the Catapres-TTS® contains aluminum, it is recommended to remove the system before undergoing an MRI.

Information for Patients

Patients should be cautioned against interruption of Catapres‑TTS® (clonidine transdermal system) therapy without their physician’s advice.

Since patients may experience a possible sedative effect, dizziness, or accommodation disorder with use of clonidine, caution patients about engaging in activities such as driving a vehicle or operating appliances or machinery. Also, inform patients that this sedative effect may be increased by concomitant use of alcohol, barbiturates, or other sedating drugs.

Patients who wear contact lenses should be cautioned that treatment with Catapres-TTS® may cause dryness of eyes.

Patients should be instructed to consult their physicians promptly about the possible need to remove the patch if they observe moderate to severe localized erythema and/or vesicle formation at the site of application or generalized skin rash.

If a patient experiences isolated, mild localized skin irritation before completing 7 days of use, the system may be removed and replaced with a new system applied to a fresh skin site.

If the system should begin to loosen from the skin after application, the patient should be instructed to place the adhesive cover directly over the system to ensure adhesion during its 7‑day use.

Used Catapres‑TTS® patches contain a substantial amount of their initial drug content which may be harmful to infants and children if accidentally applied or ingested. THEREFORE, PATIENTS SHOULD BE CAUTIONED TO KEEP BOTH USED AND UNUSED CATAPRES‑TTS® PATCHES OUT OF THE REACH OF CHILDREN. After use, CATAPRES‑TTS should be folded in half with the adhesive sides together and discarded away from children’s reach.

Instructions for use, storage and disposal of the system are provided at the end of this monograph. These instructions are also included in each box of Catapres‑TTS®.

Drug Interactions

Clonidine may potentiate the CNS-depressive effects of alcohol, barbiturates or other sedating drugs. If a patient receiving clonidine is also taking tricyclic antidepressants, the hypotensive effect of clonidine may be reduced, necessitating an increase in the clonidine dose. If a patient receiving clonidine is also taking neuroleptics, orthostatic regulation disturbances (e.g., orthostatic hypotension, dizziness, fatigue) may be induced or exacerbated.

Monitor heart rate in patients receiving clonidine concomitantly with agents known to affect sinus node function or AV nodal conduction e.g., digitalis, calcium channel blockers, and beta‑blockers. Sinus bradycardia resulting in hospitalization and pacemaker insertion has been reported in association with the use of clonidine concomitantly with diltiazem or verapamil.

Amitriptyline in combination with clonidine enhances the manifestation of corneal lesions in rats (see Toxicology).

Toxicology

In several studies with oral clonidine hydrochloride, a dose-dependent increase in the incidence and severity of spontaneous retinal degeneration was seen in albino rats treated for six months or longer. Tissue distribution studies in dogs and monkeys showed a concentration of clonidine in the choroid.

In view of the retinal degeneration seen in rats, eye examinations were performed during clinical trials in 908 patients before, and periodically after, the start of clonidine therapy. In 353 of these 908 patients, the eye examinations were carried out over periods of 24 months or longer. Except for some dryness of the eyes, no drug‑related abnormal ophthalmological findings were recorded and, according to specialized tests such as electroretinography and macular dazzle, retinal function was unchanged.

In combination with amitriptyline, clonidine hydrochloride administration led to the development of corneal lesions in rats within 5 days.

Carcinogenesis, Mutagenesis, Impairment of Fertility

Chronic dietary administration of clonidine was not carcinogenic to rats (132 weeks) or mice (78 weeks) dosed, respectively, at up to 46 to 70 times the maximum recommended daily human dose as mg/kg (9 or 6 times the MRDHD on a mg/m^2 basis). There was no evidence of genotoxicity in the Ames test for mutagenicity or mouse micronucleus test for clastogenicity.

Fertility of male and female rats was unaffected by clonidine doses as high as 150 µg/kg (approximately 3 times the MRDHD). In a separate experiment, fertility of female rats appeared to be affected at dose levels of 500 to 2000 µg/kg (10 to 40 times the oral MRDHD on a mg/kg basis; 2 to 8 times the MRDHD on a mg/m^2 basis).

Pregnancy

Teratogenic Effects

Reproduction studies performed in rabbits at doses up to approximately 3 times the oral maximum recommended daily human dose (MRDHD) of Catapres® (clonidine hydrochloride) produced no evidence of a teratogenic or embryotoxic potential in rabbits. In rats, however, doses as low as 1/3 the oral MRDHD (1/15 the MRDHD on a mg/m^2 basis) of clonidine were associated with increased resorptions in a study in which dams were treated continuously from 2 months prior to mating. Increased resorptions were not associated with treatment at the same or at higher dose levels (up to 3 times the oral MRDHD) when the dams were treated on gestation days 6 to 15. Increases in resorption were observed at much higher dose levels (40 times the oral MRDHD on a mg/kg basis; 4 to 8 times the MRDHD on a mg/m^2 basis) in mice and rats treated on gestation days 1 to 14 (lowest dose employed in the study was 500 µg/kg).

No adequate well‑controlled studies have been conducted in pregnant women. Clonidine crosses the placental barrier (see CLINICAL PHARMACOLOGY, Pharmacokinetics). Because animal reproduction studies are not always predictive of human response, this drug should be used during pregnancy only if clearly needed.

Nursing Mothers

As clonidine is excreted in human milk, caution should be exercised when Catapres‑TTS® is administered to a nursing woman.

Pediatric Use

Safety and effectiveness in pediatric patients have not been established in adequate and well-controlled trials.

ADVERSE REACTIONS

Clinical trial experience with Catapres-TTS®

Most systemic adverse effects during Catapres-TTS® therapy have been mild and have tended to diminish with continued therapy. In a 3‑month multi-clinic trial of Catapres-TTS® in 101 hypertensive patients, the systemic adverse reactions were, dry mouth (25 patients) and drowsiness (12), fatigue (6), headache (5), lethargy and sedation (3 each), insomnia, dizziness, impotence/sexual dysfunction, dry throat (2 each) and constipation, nausea, change in taste and nervousness (1 each).

In the above mentioned 3‑month controlled clinical trial, as well as other uncontrolled clinical trials, the most frequent adverse reactions were dermatological and are described below.

In the 3‑month trial, 51 of the 101 patients had localized skin reactions such as erythema (26 patients) and/or pruritus, particularly after using an adhesive cover throughout the 7‑day dosage interval. Allergic contact sensitization to Catapres‑TTS® was observed in 5 patients. Other skin reactions were localized vesiculation (7 patients), hyperpigmentation (5), edema (3), excoriation (3), burning (3), papules (1), throbbing (1), blanching (1), and a generalized macular rash (1).

In additional clinical experience, contact dermatitis resulting in treatment discontinuation was observed in 128 of 673 patients (about 19 in 100) after a mean duration of treatment of 37 weeks. The incidence of contact dermatitis was about 34 in 100 among white women, about 18 in 100 in white men, about 14 in 100 in black women, and approximately 8 in 100 in black men. Analysis of skin reaction data showed that the risk of having to discontinue Catapres‑TTS® treatment because of contact dermatitis was greatest between treatment weeks 6 and 26, although sensitivity may develop either earlier or later in treatment.

In a large‑scale clinical acceptability and safety study by 451 physicians in a total of 3539 patients, other allergic reactions were recorded for which a causal relationship to Catapres‑TTS® was not established: maculopapular rash (10 cases); urticaria (2 cases); and angioedema of the face (2 cases), which also affected the tongue in one of the patients.

Marketing Experience with Catapres-TTS®

The following adverse reactions have been identified during post-approval use of Catapres-TTS®. Because these reactions are reported voluntarily from a population of uncertain size, it is not always possible to estimate reliably their frequency or establish a causal relationship to drug exposure. Decisions to include these reactions in labeling are typically based on one or more of the following factors: (1) seriousness of the reaction, (2) frequency of reporting, or (3) strength of causal connection to Catapres-TTS®.

Body as a Whole: Fever; malaise; weakness; pallor; and withdrawal syndrome.

Cardiovascular: Congestive heart failure; cerebrovascular accident; electrocardiographic abnormalities (i.e., bradycardia, sick sinus syndrome disturbances and arrhythmias); chest pain; orthostatic symptoms; syncope; increases in blood pressure; sinus bradycardia and AV block with and without the use of concomitant digitalis; Raynaud’s phenomenon; tachycardia; bradycardia; and palpitations.

Central and Peripheral Nervous System/Psychiatric: Delirium; mental depression; hallucinations (including visual and auditory); localized numbness; vivid dreams or nightmares; restlessness; anxiety; agitation; irritability; other behavioral changes; and drowsiness.

Dermatological: Angioneurotic edema; localized or generalized rash; hives; urticaria; contact dermatitis; pruritus; alopecia; and localized hypo or hyper pigmentation.

Gastrointestinal: Anorexia and vomiting.

Genitourinary: Difficult micturition; loss of libido; and decreased sexual activity.

Metabolic: Gynecomastia or breast enlargement and weight gain.

Musculoskeletal: Muscle or joint pain; and leg cramps.

Ophthalmological: Blurred vision; burning of the eyes and dryness of the eyes.

Adverse Events Associated with Oral CATAPRES® Therapy: Most adverse effects are mild and tend to diminish with continued therapy. The most frequent (which appear to be dose-related) are dry mouth, occurring in about 40 of 100 patients; drowsiness, about 33 in 100; dizziness, about 16 in 100; constipation and sedation, each about 10 in 100. The following less frequent adverse experiences have also been reported in patients receiving CATAPRES® (clonidine hydrochloride, USP) tablets, but in many cases patients were receiving concomitant medication and a causal relationship has not been established.

Body as a Whole: Fatigue, fever, headache, pallor, weakness, and withdrawal syndrome. Also reported were a weakly positive Coombs’ test and increased sensitivity to alcohol.

Cardiovascular: Bradycardia, congestive heart failure, electrocardiographic abnormalities (i.e., sinus node arrest, junctional bradycardia, high degree AV block and arrhythmias), orthostatic symptoms, palpitations, Raynaud’s phenomenon, syncope, and tachycardia. Cases of sinus bradycardia and AV block have been reported, both with and without the use of concomitant digitalis.

Central Nervous System: Agitation, anxiety, delirium, delusional perception, hallucinations (including visual and auditory), insomnia, mental depression, nervousness, other behavioral changes, paresthesia, restlessness, sleep disorder, and vivid dreams or nightmares.

Dermatological: Alopecia, angioneurotic edema, hives, pruritus, rash, and urticaria.

Gastrointestinal: Abdominal pain, anorexia, constipation, hepatitis, malaise, mild transient abnormalities in liver function tests, nausea, parotitis, pseudo-obstruction (including colonic pseudo-obstruction), salivary gland pain, and vomiting.

Genitourinary: Decreased sexual activity, difficulty in micturition, erectile dysfunction, loss of libido, nocturia, and urinary retention.

Hematologic: Thrombocytopenia.

Metabolic: Gynecomastia, transient elevation of blood glucose or serum creatine phosphokinase, and weight gain.

Musculoskeletal: Leg cramps and muscle or joint pain.

Oro-otolaryngeal: Dryness of the nasal mucosa.

Ophthalmological: Accommodation disorder, blurred vision, burning of the eyes, decreased lacrimation, and dryness of the eyes.

OVERDOSAGE

Hypertension may develop early and may be followed by hypotension, bradycardia, respiratory depression, hypothermia, drowsiness, decreased or absent reflexes, weakness, irritability and miosis. The frequency of CNS depression may be higher in children than adults. Large overdoses may result in reversible cardiac conduction defects or dysrhythmias, apnea, coma and seizures. Signs and symptoms of overdose generally occur within 30 minutes to two hours after exposure. As little as 0.1 mg of clonidine has produced signs of toxicity in children.

If symptoms of poisoning occur following dermal exposure, remove all Catapres‑TTS® transdermal systems. After their removal, the plasma clonidine levels will persist for about 8 hours, then decline slowly over a period of several days. Rare cases of Catapres‑TTS® poisoning due to accidental or deliberate mouthing or ingestion of the patch have been reported, many of them involving children.

There is no specific antidote for clonidine overdosage. Ipecac syrup‑induced vomiting and gastric lavage would not be expected to remove significant amounts of clonidine following dermal exposure. If the patch is ingested, whole bowel irrigation may be considered and the administration of activated charcoal and/or cathartic may be beneficial. Supportive care may include atropine sulfate for bradycardia, intravenous fluids and/or vasopressor agents for hypotension and vasodilators for hypertension. Naloxone may be a useful adjunct for the management of clonidine‑induced respiratory depression, hypotension and/or coma; blood pressure should be monitored since the administration of naloxone has occasionally resulted in paradoxical hypertension. Dialysis is not likely to significantly enhance the elimination of clonidine.

The largest overdose reported to date, involved a 28‑year old male who ingested 100 mg of clonidine hydrochloride powder. This patient developed hypertension followed by hypotension, bradycardia, apnea, hallucinations, semicoma, and premature ventricular contractions. The patient fully recovered after intensive treatment. Plasma clonidine levels were 60 ng/mL after 1 hour, 190 ng/mL after 1.5 hours, 370 ng/mL after 2 hours, and 120 ng/mL after 5.5 and 6.5 hours. In mice and rats, the oral LD50 of clonidine is 206 and 465 mg/kg, respectively.

DOSAGE AND ADMINISTRATION

Apply Catapres‑TTS® (clonidine transdermal system) once every 7 days to a hairless area of intact skin on the upper outer arm or chest. Each new application of Catapres‑TTS® should be on a different skin site from the previous location. If the system loosens during 7‑day wearing, the adhesive cover should be applied directly over the system to ensure good adhesion. There have been rare reports of the need for patch changes prior to 7 days to maintain blood pressure control.

To initiate therapy, Catapres‑TTS® dosage should be titrated according to individual therapeutic requirements, starting with Catapres‑TTS®-1. If after one or two weeks the desired reduction in blood pressure is not achieved, increase the dosage by adding another Catapres‑TTS®-1 or changing to a larger system. An increase in dosage above two Catapres‑TTS®-3 is usually not associated with additional efficacy.

When substituting Catapres‑TTS® for oral clonidine or for other antihypertensive drugs, physicians should be aware that the antihypertensive effect of Catapres‑TTS® may not commence until 2‑3 days after initial application. Therefore, gradual reduction of prior drug dosage is advised. Some or all previous antihypertensive treatment may have to be continued, particularly in patients with more severe forms of hypertension.

Renal Impairment

Patients with renal impairment may benefit from a lower initial dose. Patients should be carefully monitored. Since only a minimal amount of clonidine is removed during routine hemodialysis, there is no need to give supplemental clonidine following dialysis.

HOW SUPPLIED

Catapres‑TTS®-1, Catapres‑TTS®-2, and Catapres-TTS®-3 are supplied as 4 pouched systems and 4 adhesive covers per carton. See chart below.

 | Programmed Delivery Clonidine in vivo
 | Per Day Over 1 Week | Clonidine Content | Size | Code
Catapres-TTS®-1 (clonidine transdermal system) NDC 82089-101-34 | 0.1 mg | 2.5 mg | 3.5 cm^2 | BI-31
Catapres-TTS®-2 (clonidine transdermal system) NDC 82089-102-34 | 0.2 mg | 5.0 mg | 7.0 cm^2 | BI-32
Catapres-TTS®-3 (clonidine transdermal system) NDC 82089-103-34 | 0.3 mg | 7.5 mg | 10.5 cm^2 | BI-33

STORAGE AND HANDLING

Store at 25°C (77°F); excursions permitted to 15°- 30°C (59°- 86°F) [see USP Controlled Room Temperature].

Manufactured by:
Alza Corporation,
Vacaville, CA 95688, USA

Catapres-TTS® is a registered trademark of Boehringer Ingelheim International GmbH used under license

Address medical inquiries to: (866) 380-1080

Copyright © 2021 Technomed Inc.
ALL RIGHTS RESERVED

Revised: March 2023

222068/C

PATIENT INSTRUCTIONS

Catapres-TTS®
(clonidine transdermal system)

(Read the following instructions carefully before using this medication. If you have any questions, please consult with your doctor.)

General Information

Catapres‑TTS® (clonidine transdermal system) is a square, tan adhesive PATCH containing an active blood‑pressure‑lowering medication. It is designed to deliver the drug into the body through the skin smoothly and consistently for one full week. Normal exposure to water, as in showering, bathing, and swimming, should not affect the PATCH.

The optional white, round ADHESIVE COVER should be applied directly over the PATCH, should the PATCH begin to separate from the skin. The ADHESIVE COVER ensures that the PATCH sticks to the skin. The Catapres‑TTS® PATCH must be replaced with a new one on a fresh skin site if the one in use significantly loosens or falls off.

Skin burns have been reported at the patch site in several patients wearing an aluminized transdermal system during a magnetic resonance imaging scan (MRI). Because the Catapres-TTS® PATCH contains aluminum, it is recommended to remove the system before undergoing an MRI.

Each box of Catapres-TTS® contains two types of pouches:

Figure 2

How to Apply the Catapres-TTS® PATCH

1. Apply the square, tan Catapres‑TTS® PATCH once a week, preferably at a convenient time on the same day of the week (i.e., prior to bedtime on Tuesday of week one; prior to bedtime on Tuesday of week two, etc.).
2. Select a hairless area such as on the upper, outer arm or upper chest. The area chosen should be free of cuts, abrasions, irritation, scars or calluses and should not be shaved before applying the Catapres‑TTS® PATCH. Do not place the Catapres‑TTS® PATCH on skin folds or under tight undergarments, since premature loosening may occur.
3. Wash hands with soap and water and thoroughly dry them.
4. Clean the area chosen with soap and water. Rinse and wipe dry with a clean, dry tissue.
5. Select the pouch with the red and orange colors labeled Catapres-TTS® and open it as illustrated in Figure 3. Remove the square, tan PATCH from the pouch.

Figure 3

6. Remove the clear plastic protective backing from the PATCH by gently peeling off one half of the backing at a time as shown in Figure 4. Avoid touching the sticky side of the Catapres‑TTS®PATCH.

Figure 4

7. Place the Catapres‑TTS® PATCH on the prepared skin site (sticky side down) by applying firm pressure over the PATCH to ensure good contact with the skin, especially around the edges (Figure 5). Discard the clear plastic protective backing and wash your hands with soap and water to remove any drug from your hands.

Figure 5

8. After one week, remove the old PATCH and discard it (refer to Instructions for Disposal). After choosing a different skin site, repeat instructions 2 through 7 for the application of your next Catapres‑TTS® PATCH.

What to do if your Catapres-TTS® PATCH becomes loose while wearing:

How to Apply the ADHESIVE COVER

Note: The white, round, ADHESIVE COVER does not contain any drug and should not be used alone. The COVER should be applied directly over the Catapres‑TTS® PATCH only if the PATCH begins to separate from the skin, thereby ensuring that it sticks to the skin for seven full days.

1. Wash hands with soap and water and thoroughly dry them.
2. Using a clean, dry tissue, make sure that the area around the square, tan Catapres-TTS® PATCH is clean and dry. Press gently on the Catapres‑TTS® PATCH to ensure that the edges are in good contact with the skin.
3. Take the white, round, ADHESIVE COVER (Figure 6) from the plain white pouch and remove the paper liner backing from the COVER.
4. Carefully center the round, white ADHESIVE COVER over the square, tan Catapres‑TTS® PATCH and apply firm pressure, especially around the edges in contact with the skin.

How should I store the Catapres-TTS® PATCH?
Store the Catapres-TTS® PATCH at room temperature 68°F to 77°F (20°C to 25°C)

Instructions for Disposal
KEEP OUT OF REACH OF CHILDREN

During or even after use, a PATCH contains active medication which may be harmful to infants and children if accidentally applied or ingested. After use, fold in half with the sticky sides together. Dispose of carefully out of reach of children.

Manufactured by:
Alza Corporation,
Vacaville, CA 95688 USA

Catapres-TTS® is a registered trademark of Boehringer Ingelheim International GmbH used under license

Copyright © 2021 Technomed Inc.
ALL RIGHTS RESERVED

Revised: March 2023

222068/C

PRINCIPAL DISPLAY PANEL - 0.1 mg Carton

NDC 82089-101-34

Catapres-TTS®-1
(clonidine transdermal system)

4 Systems and 4 Adhesive Covers

Programmed delivery in vivo of 0.1 mg clonidine

per day for one week.

Rx only

For Transdermal Use Only -

See package insert for dosage information

PRINCIPAL DISPLAY PANEL - 0.1 mg Adhesive Cover

Contents: 1 ADHESIVE COVER

WARNING

THIS DOES NOT CONTAIN

ACTIVE MEDICATION.

APPLY OVER THE PATCH,

IF NECESSARY.

1

PRINCIPAL DISPLAY PANEL - 0.1 mg Pouch

Catapres-TTS®-1

(clonidine transdermal system)

Programmed delivery in vivo of 0.1 mg clonidine

per day for one week.

To avoid possible burns, remove the

Catapres-TTS® patch before

undergoing an MRI (magnetic

resonance imaging) procedure.

Rx only

222060

PRINCIPAL DISPLAY PANEL - 0.2 mg Carton

NDC 82089-102-34

Catapres-TTS®-2
(clonidine transdermal system)

4 Systems and 4 Adhesive Covers

Programmed delivery in vivo of 0.2 mg clonidine

per day for one week.

Rx only

For Transdermal Use Only -

See package insert for dosage information

PRINCIPAL DISPLAY PANEL - 0.2 mg Adhesive Cover

Contents: 1 ADHESIVE COVER

WARNING

THIS DOES NOT CONTAIN

ACTIVE MEDICATION.

APPLY OVER THE PATCH,

IF NECESSARY.

2

PRINCIPAL DISPLAY PANEL - 0.2 mg Pouch

Catapres-TTS®-2

(clonidine transdermal system)

Programmed delivery in vivo of 0.2 mg clonidine

per day for one week.

To avoid possible burns, remove the

Catapres-TTS® patch before

undergoing an MRI (magnetic

resonance imaging) procedure.

Rx only

222063

PRINCIPAL DISPLAY PANEL carton - 0.3 mg

NDC 82089-103-34

Catapres-TTS®-3
(clonidine transdermal system)

4 Systems and 4 Adhesive Covers

Programmed delivery in vivo of 0.3 mg clonidine

per day for one week.

Rx only

For Transdermal Use Only -

See package insert for dosage information

PRINCIPAL DISPLAY PANEL - 0.3 mg Adhesive Cover

Contents: 1 ADHESIVE COVER

WARNING

THIS DOES NOT CONTAIN

ACTIVE MEDICATION.

APPLY OVER THE PATCH,

IF NECESSARY.

3

PRINCIPAL DISPLAY PANEL - 0.3 mg Pouch

Catapres-TTS®-3
(clonidine transdermal system)

Programmed delivery in vivo of 0.3 mg clonidine

per day for one week.

To avoid possible burns, remove the

Catapres-TTS® patch before

undergoing an MRI (magnetic

resonance imaging) procedure.

Rx only

222066